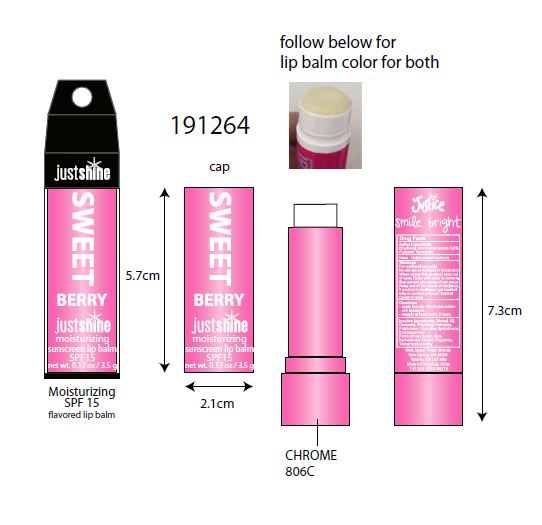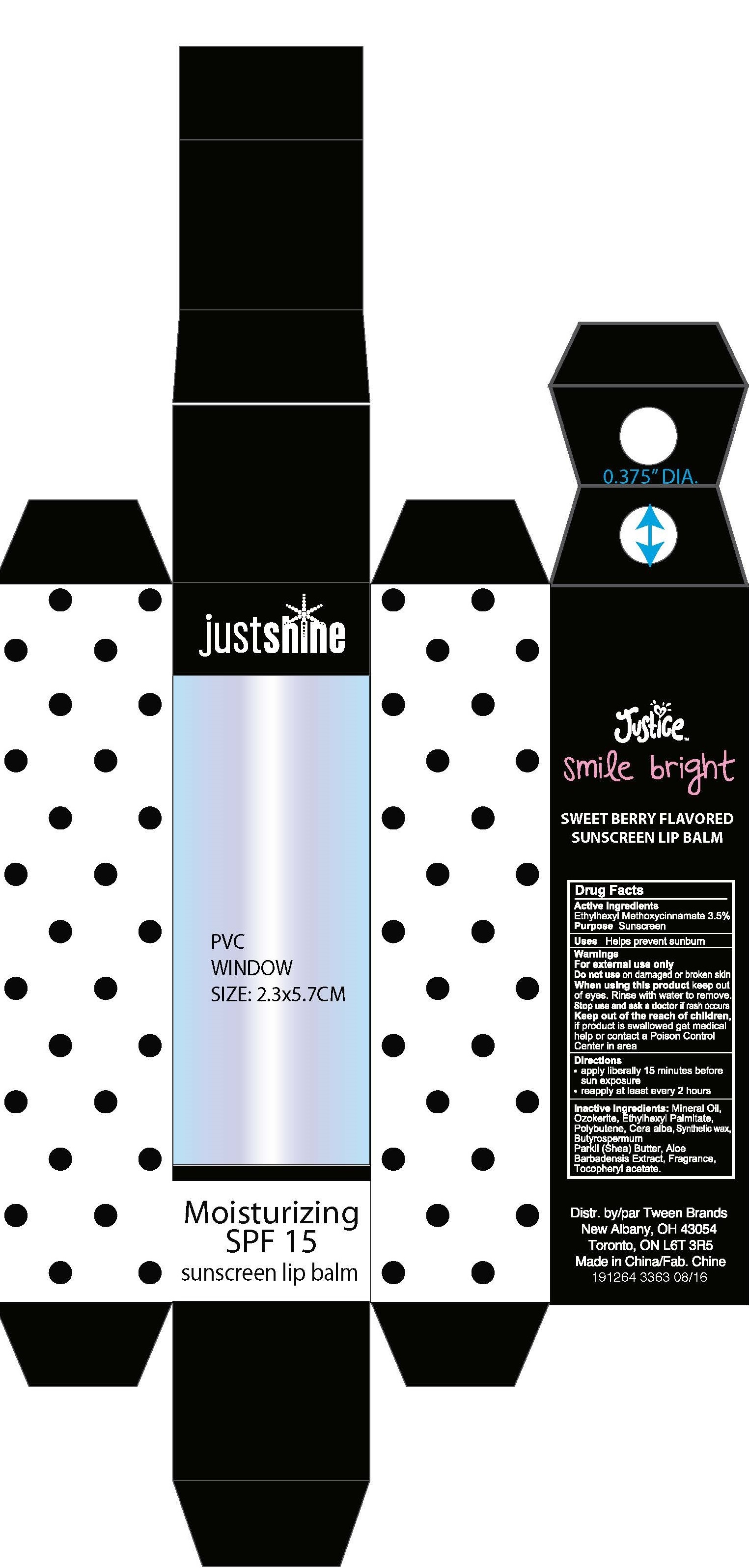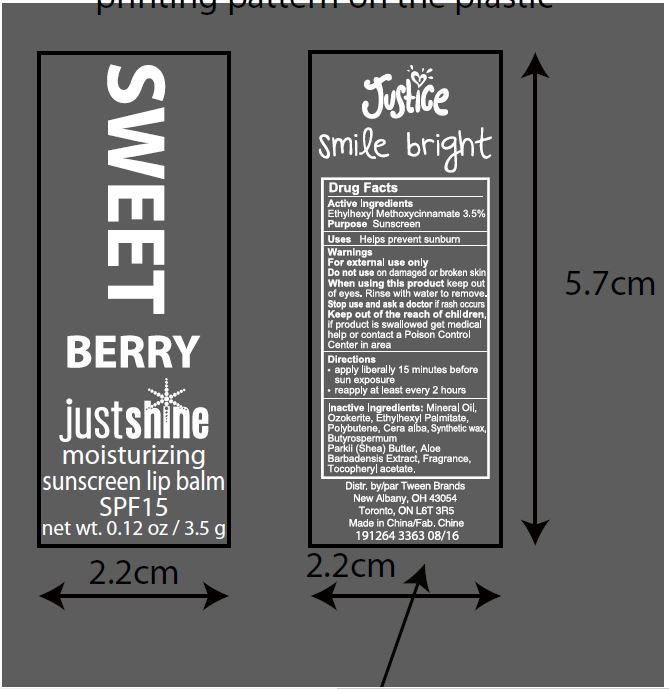 DRUG LABEL: Sweet Berry Moisturizing Sunscreen Lip Balm SPF 15
NDC: 60637-115 | Form: LIPSTICK
Manufacturer: Tween Brands Inc
Category: otc | Type: HUMAN OTC DRUG LABEL
Date: 20160906

ACTIVE INGREDIENTS: OCTINOXATE 122.5 mg/3.5 g
INACTIVE INGREDIENTS: CERESIN; ETHYLHEXYL PALMITATE; SHEA BUTTER; .ALPHA.-TOCOPHEROL ACETATE; MINERAL OIL

Sweet Berry Moisturizing Sunscreen Lip Balm SPF 15

Active Ingredient

Ethylhexyl Methoxycinnamate 3.5%

Purpose

Sunscreen

Uses

Helps prevent sunburn

Warning

- For external Use only
- Do not use on damaged or broken skin.
- When using this product keep out of eyes.
- Rinse with water to remove.
- Stop use and ask a doctor if rash occurs.

Keep out of the reach of children

If product is swallowed get medical help or contact a Poison Control Center in area.

Directions

- Apply liberally 15 minutes before sun exposure.
- Reapply at least every 2 hours.

Inactive Ingredients

Mineral Oil, Ozokerite, Ethylhexyl Palmitate, Polybutene, Cera alba, Synthetic wax, Butyrospermum Parkii (Shea) Butter, Aloe Barbadensis Extract, Fragrance, Tocopheryl acerare.